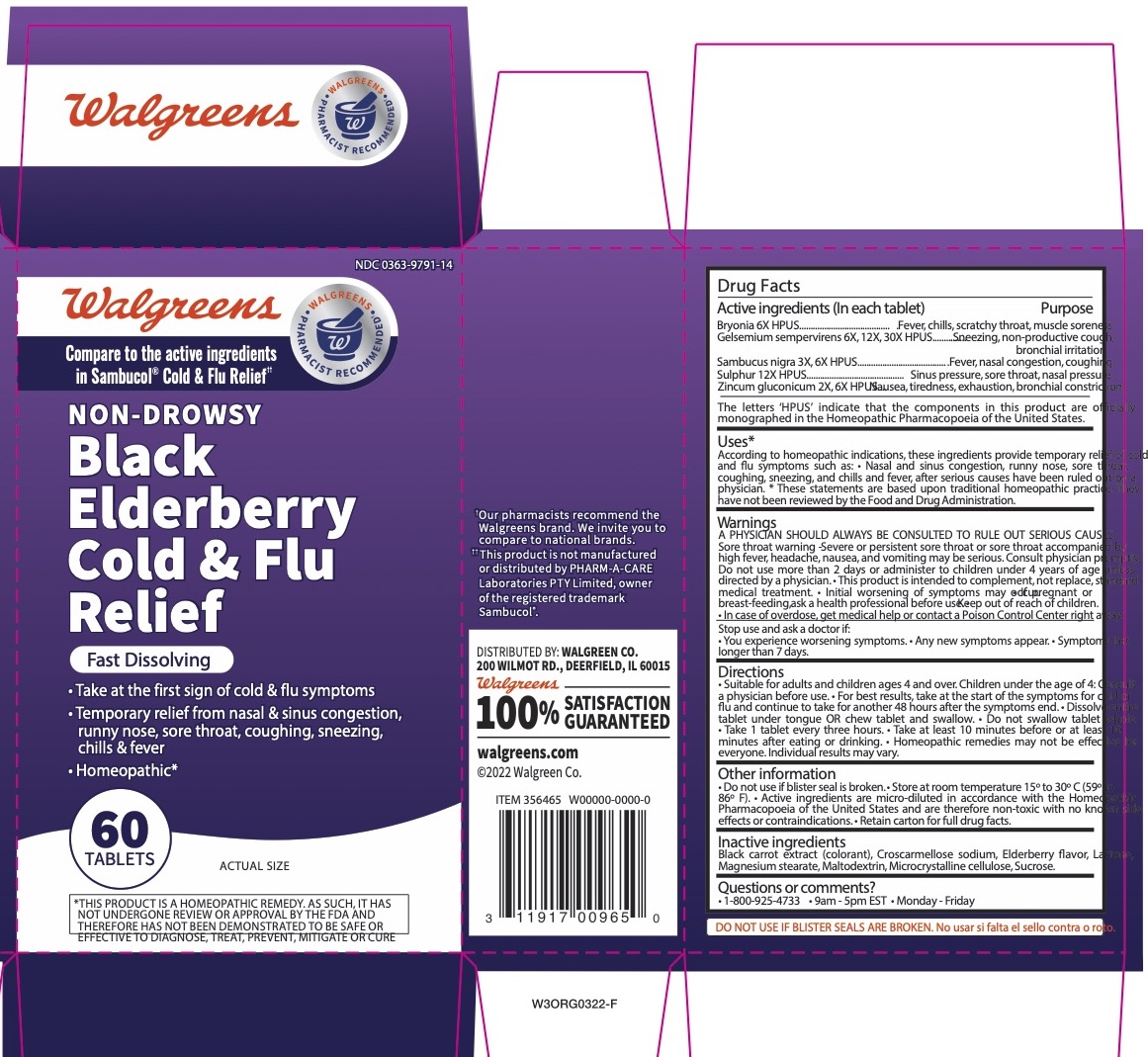 DRUG LABEL: Walgreens Black Elderberry Cold and Flu Relief
NDC: 0363-9791 | Form: TABLET, ORALLY DISINTEGRATING
Manufacturer: Walgreen Co.
Category: homeopathic | Type: HUMAN OTC DRUG LABEL
Date: 20251217

ACTIVE INGREDIENTS: ZINC GLUCONATE 2 [hp_X]/1 1; SULFUR 12 [hp_X]/1 1; SAMBUCUS NIGRA FLOWERING TOP 3 [hp_X]/1 1; GELSEMIUM SEMPERVIRENS ROOT 6 [hp_X]/1 1; BRYONIA ALBA ROOT 6 [hp_X]/1 1
INACTIVE INGREDIENTS: LACTOSE, UNSPECIFIED FORM; BLACK CARROT ANTHOCYANINS; MAGNESIUM STEARATE; SUCROSE; MICROCRYSTALLINE CELLULOSE; EUROPEAN ELDERBERRY JUICE; CROSCARMELLOSE SODIUM

Walgreens Black Elderberry Cold and Flu Relief

Active Ingredients

Active ingredients (In each tablet) *

Bryonia 6X HPUS
Gelsemium sempervirens 6X, 12X, 30X HPUS

Sambucus nigra 3X, 6X HPUS
Sulphur 12X HPUS
Zincum gluconicum 2X, 6X HPUS

*The letters ‘HPUS’ indicate that the components in this product are officially monographed in the Homeopathic Pharmacopoeia of the United States.

Purpose

Bryonia HPUS - Fever, chills, scratchy throat, muscle soreness
Gelsemium sempervirens HPUS - Sneezing, non-productive cough, bronchial irritation

Sambucus nigra HPUS - Fever, nasal congestion, coughing
Sulphur HPUS - Sinus pressure, sore throat, nasal pressure
Zincum gluconicum HPUS - Nausea, tiredness, exhaustion, bronchial constriction

Uses*

According to homeopathic indications, these ingredients provide temporary relief of cold and flu symptoms such as: • Nasal and sinus congestion, runny nose, sor coughing, sneezing, and chills and fever, after serious causes have been ruled out by a physician.

* These statements are based upon traditional homeopathic practice. They have not been reviewed by the Food and Drug Administration.

Warnings

A PHYSICIAN SHOULD ALWAYS BE CONSULTED TO RULE OUT SERIOUS CAUSES.

Sore throat warning - Severe or persistent sore throat or sore throat accompanied by high fever, headache, nausea, and vomiting may be serious. Consult phys Do not use more than 2 days or administer to children under 4 years of age unless directed by a physician. • This product is intended to complement, not replace, medical treatment. • Initial worsening of symptoms may occur.

Pregnant or breast-feeding

• If pregnant or breast-feeding, ask a health professional before use.

• Keep out of reach of children. • In case of overdose, get medical help or contact a Poison Control Center right away.

Stop use

Stop use and ask a doctor if:
• You experience worsening symptoms. • Any new symptoms appear. • Symptoms last longer than 7 days.

Directions

• Suitable for adults and children ages 4 and over. Children under the age of 4: Consult a physician before use. • For best results, take at the start of the symptoms for cold or flu and continue to take for another 48 hours after the symptoms end. • Dissolve entire tablet under tongue OR chew tablet and swallow. • Do not swallow tablet whole. • Take 1 tablet every three hours. • Take at least 10 minutes before or at least 10 minutes after eating or drinking. • Homeopathic remedies may not be effective for everyone. Individual results may vary.

Other information

• Do not use if blister seal is broken. • Store at room temperature 15o to 30o C (59o to 86o F). • Active ingredients are micro-diluted in accordance with the Pharmacopoeia of the United States and are therefore non-toxic with no known side effects or contraindications. • Retain carton for full drug facts.

Inactive ingredients

Black carrot extract (colorant), Croscarmellose sodium, Elderberry flavor, Lactose, Magnesium stearate, Maltodextrin, Microcrystalline cellulose, Sucrose.

Questions or comments?

•1-800-925-4733 •9am-5pmEST•Monday-Friday